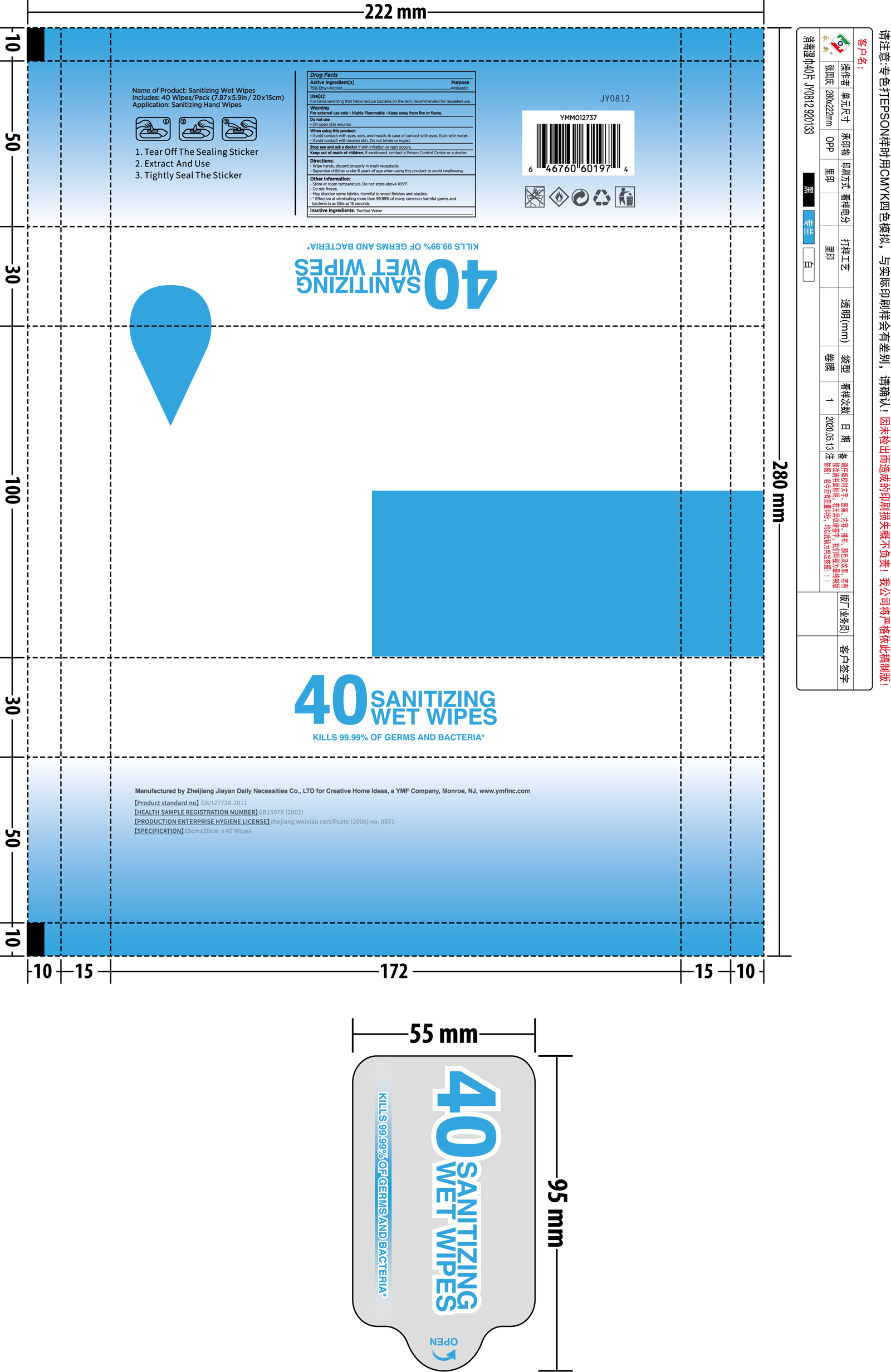 DRUG LABEL: sanitizing wipes
NDC: 78198-001 | Form: CLOTH
Manufacturer: Y M F Carpets, Inc.
Category: otc | Type: HUMAN OTC DRUG LABEL
Date: 20200625

ACTIVE INGREDIENTS: ALCOHOL 0.75 mL/1 1
INACTIVE INGREDIENTS: WATER

sanitizing wipes

Active Ingredient(s)

Alcohol 75%. Purpose: Antiseptic

Purpose

Antiseptic

Use

For hand sanitizing that helps reduce bacteria on the skin, recommended for repeated use

Warnings

For external use only. Highly Flammable. Keep away from heat or flame

Do not use

on open skin wounds

When using this product

- Avoid contact with eyes, ears, and mouth. In case of contact with eyes, flush with water.

- Avoid contact with broken skin. Do not inhale or ingest.

Stop use and ask a doctor

if skin irritation or rash occurs.

Keep out of reach of children. If swallowed, get medical help or contact a Poison Control Center right away.

Directions

Wipe hands, discard properly in trash receptacle.

Supervise children under 6 years of age when using this product to avoid swallowing

Other information

Store at room temperature. Do not store above 105F

Do not freeze.

May discolor some fabrics. Harmful to wood finishes and plastics.

Effective at eliminating more than 99.99% of many common harmful germs and bacteria in as little as 15 seconds

Inactive ingredients

Purified water

Package Label - Principal Display Panel

40 PCS NDC: 78198-001-01